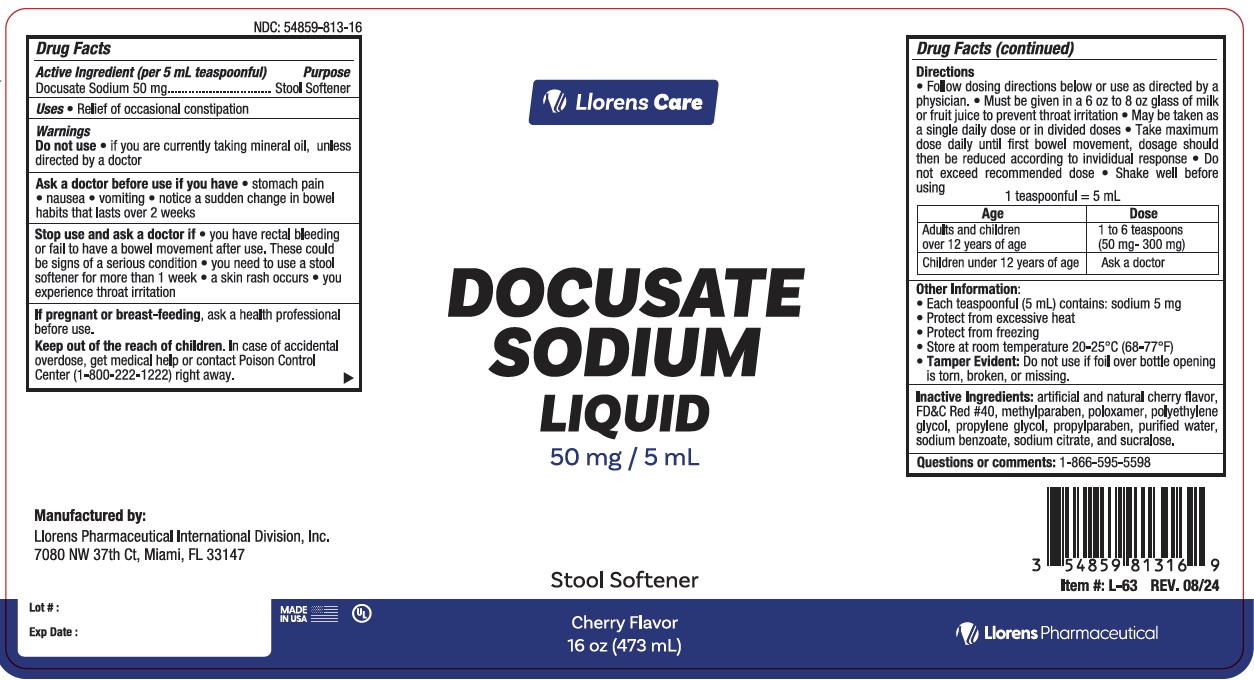 DRUG LABEL: Docusate Sodium Liquid
NDC: 54859-813 | Form: LIQUID
Manufacturer: LLORENS PHARMACEUTICALS INTERNATIONAL DIVISION
Category: otc | Type: HUMAN OTC DRUG LABEL
Date: 20251231

ACTIVE INGREDIENTS: DOCUSATE SODIUM 50 mg/5 mL
INACTIVE INGREDIENTS: WATER; SODIUM BENZOATE; SODIUM CITRATE; SUCRALOSE; FD&C RED NO. 40; METHYLPARABEN; POLOXAMER 124; POLYETHYLENE GLYCOL, UNSPECIFIED; PROPYLENE GLYCOL; PROPYLPARABEN

Llorens-Ducosate Sodium 813

Active Ingredients (per 5 mL)

Docusate Sodium 50 mg

Purpose

Stool Softener

Uses

Relief of occasional constipation

Warnings

Do not use when

- abdominal pain, nausea, or vomiting are present unless directed by a doctor
- for more than one week unless directed by a doctor

Ask a doctore before use if you

- are taking mineral oil
- have noticed a sudden change in bowel habits that last more than two weeks

Stop use and ask doctor if

- you have no bowel movements within 3 days
- you have rectal bleeding
- these could be signs of a serious condition
- a skin rash occurs
- you experience throat irritation

PREGNANCY OR BREAST FEEDING

If pregnant or breast-feeding, ask a doctor before use

Keep out of reach of children. In case of accidental overdose, seek medical assistance or contact a Poison Control Center right away.

Directions

- follow dosing directions below or use as directed by a physician
- must be given in a 6 oz to 8 oz glass of milk or fruit juice to prevent throat irritation
- may be taken as a single daily dose or in dividend dose
- take maximum dose daily until first bowel movement, dosage should then be reduced according to individual response
- do not exceed recommended dose
- shake well before using

1 teasponnful = 5 mL

Age | Dose
Adults and children over 12 years of age | 1 to 6 teaspoons (50 mg - 300 mg)
Children under 12 years of age | Ask a doctor

INACTIVE INGREDIENT

Inactive ingredients: FD&C red #40, flavor, methylparaben, poloxamer, polyethylene glycol, propylene glycol, propylparaben, sodium benzoate, sodium citrate, sucralose

Questions or comments? 1-866-595-5598